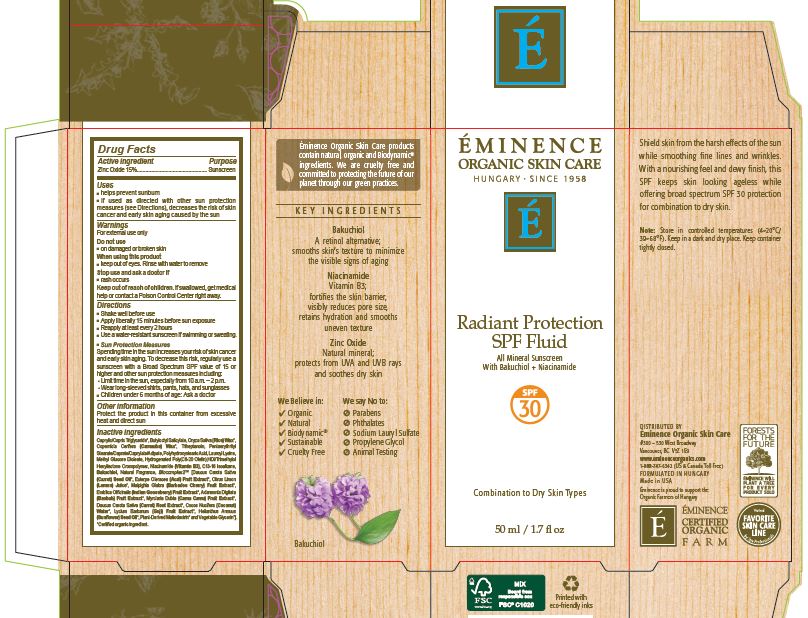 DRUG LABEL: Eminence Radiant Protection SPF Fluid
NDC: 15751-3506 | Form: LIQUID
Manufacturer: Eminence Organic Skin Care
Category: otc | Type: HUMAN OTC DRUG LABEL
Date: 20241118

ACTIVE INGREDIENTS: ZINC OXIDE 150 mg/1 mL
INACTIVE INGREDIENTS: CAPRYLIC/CAPRIC/LINOLEIC TRIGLYCERIDE; C13-16 ISOPARAFFIN; CARNAUBA WAX; POLYHYDROXYSTEARIC ACID (2300 MW); TRIHEPTANOIN; LAUROYL LYSINE; NIACINAMIDE; FRAGRANCE 13576; MALPIGHIA GLABRA FRUIT; ADANSONIA DIGITATA FRUIT; MYRCIARIA DUBIA FRUIT; DAUCUS CAROTA SUBSP. SATIVUS WHOLE; COCONUT WATER; LYCIUM BARBARUM FRUIT; BUTYLOCTYL SALICYLATE; PENTAERYTHRITYL STEARATE; METHYL GLUCOSE DIOLEATE; BAKUCHIOL; ACAI; LEMON; STARCH, TAPIOCA; THIOCTIC ACID; RICE BRAN; HYDROGENATED C6-20 POLYOLEFIN (100 CST); HEXAMETHYLENE DIISOCYANATE/TRIMETHYLOL HEXYLLACTONE CROSSPOLYMER; PHYLLANTHUS EMBLICA FRUIT; UBIDECARENONE

Radiant Protection SPF Fluid

Directions

Shake well before use

Apply liberally 15 minutes before sun exposure

Reapply at least every 2 hours

Use a water-resistant sunscreen if swimming or sweating.

Sun Protection Measures

Spending time in the sun increases your risk of skin cancer and early skin aging. To decrease this risk, regularly use a sunscreen with a Broad Spectrum SPF value of 15 or higher and other sun protection measures including:

Limit time in the sun, especially from 10 a.m. - 2 p.m.

Wear long-sleeved shirts, pants, hats, and sunglasses.

Children under 6 months of age: Ask a doctor.

WARNINGS

For external use only

Do not use on damaged or broken skin

When using this product keep out of eyes. Rinse with water to remove

Stop use and ask doctor if rash occurs

Inactive Ingredients

Caprylic/Capric Triglyceride*, Butyloctyl Salicylate, Oryza Sativa (Rice) Wax*, Copernicia Cerifera (Carnauba) Wax*, Triheptanoin, Pentaerythrityl Stearate/Caprate/Caprylate/Adipate, Polyhydroxystearic Acid, Lauroyl Lysine, Methyl Glucose Dioleate, Hydrogenated Poly(C6-20 Olefin),HDI/Trimethylol Hexyllactone Crosspolymer, Niacinamide (Vitamin B3), C13-16 Isoalkane, Bakuchiol, Natural Fragrance, Biocomplex2™ [Daucus Carota Sativa (Carrot) Seed Oil*, Euterpe Oleracea (Acai) Fruit Extract*, Citrus Limon (Lemon) Juice*, Malpighia Glabra (Barbados Cherry) Fruit Extract*, Emblica Officinalis (Indian Gooseberry) Fruit Extract*, Adansonia Digitata (Baobab) Fruit Extract*, Myrciaria Dubia (Camu Camu) Fruit Extract*, Daucus Carota Sativa (Carrot) Root Extract*, Cocos Nucifera (Coconut) Water*, Lycium Barbarum (Goji) Fruit Extract*, Helianthus Annuus (Sunflower) Seed Oil*, Plant-Derived Maltodextrin* and Vegetable Glycerin*].

Uses

helps prevent sunburn

if used as directed with other sun protection measures (see Directions), decreases the risk of skin cancer and early skin aging caused by the sun

KEEP OUT OF REACH OF CHILDREN

Keep out or reach of children. If swallowed, get medical help or contact a Poison Control Center right away.

Active Ingredient Purpose

Zinc Oxide 15%............Sunscreen

Radiant Protection SPF Fluid

Drug Facts

Active Ingredient Purpose

Zinc Oxide 15%……………………...Sunscreen

Uses

helps prevent sunburn
if used as directed with other sun protection measures (see Directions), decreases the risk of skin cancer and early skin aging caused by the sun

Warnings

For external use only

Do not use

on damaged or broken skin

When using this product

keep out of eyes. Rinse with water to remove

Stop use and ask doctor if

rash occurs

Keep out of reach of children. If swallowed, get medical help or contact a Poison Control Center right away.

Directions

Shake well before use
Apply liberally 15 minutes before sun exposure
Reapply at least every 2 hours
Use a water-resistant sunscreen if swimming or sweating.

Sun Protection Measures

Spending time in the sun increases your risk of skin cancer and early skin aging. To decrease this risk, regularly use a sunscreen with a Broad Spectrum SPF value of 15 or higher and other sun protection measures including:

Limit time in the sun, especially from 10 a.m. – 2 p.m.
Wear long-sleeved shirts, pants, hats, and sunglasses.
Children under 6 months of age: Ask a doctor.

Other information

Protect the product in this container from excessive heat and direct sun.

Inactive ingredients

Caprylic/Capric Triglyceride*, Butyloctyl Salicylate, Oryza Sativa (Rice) Wax*, Copernicia Cerifera (Carnauba) Wax*, Triheptanoin, Pentaerythrityl Stearate/Caprate/Caprylate/Adipate, Polyhydroxystearic Acid, Lauroyl Lysine, Methyl Glucose Dioleate, Hydrogenated Poly(C6-20 Olefin),

HDI/Trimethylol Hexyllactone Crosspolymer, Niacinamide (Vitamin B3), C13-16 Isoalkane, Bakuchiol, Natural Fragrance, Biocomplex2™ [Daucus Carota Sativa (Carrot) Seed Oil*, Euterpe Oleracea (Acai) Fruit Extract*, Citrus Limon (Lemon) Juice*, Malpighia Glabra (Barbados Cherry) Fruit Extract*, Emblica Officinalis (Indian Gooseberry) Fruit Extract*, Adansonia Digitata (Baobab) Fruit Extract*, Myrciaria Dubia (Camu Camu) Fruit Extract*, Daucus Carota Sativa (Carrot) Root Extract*, Cocos Nucifera (Coconut) Water*, Lycium Barbarum (Goji) Fruit Extract*, Helianthus Annuus (Sunflower) Seed Oil*, Plant-Derived Maltodextrin* and Vegetable Glycerin*].

DISTRIBUTED BY

Éminence Organic Skin Care

#300 - 530 West Broadway, Vancouver BC V5Z 1E9

www.eminenceorganics.com

1-888-747-6342 (US & Canada Toll Free)

FORMULATED IN HUNGARY / Made in USA

Refer to Radiant Protection SPF Fluid US 1.7oz